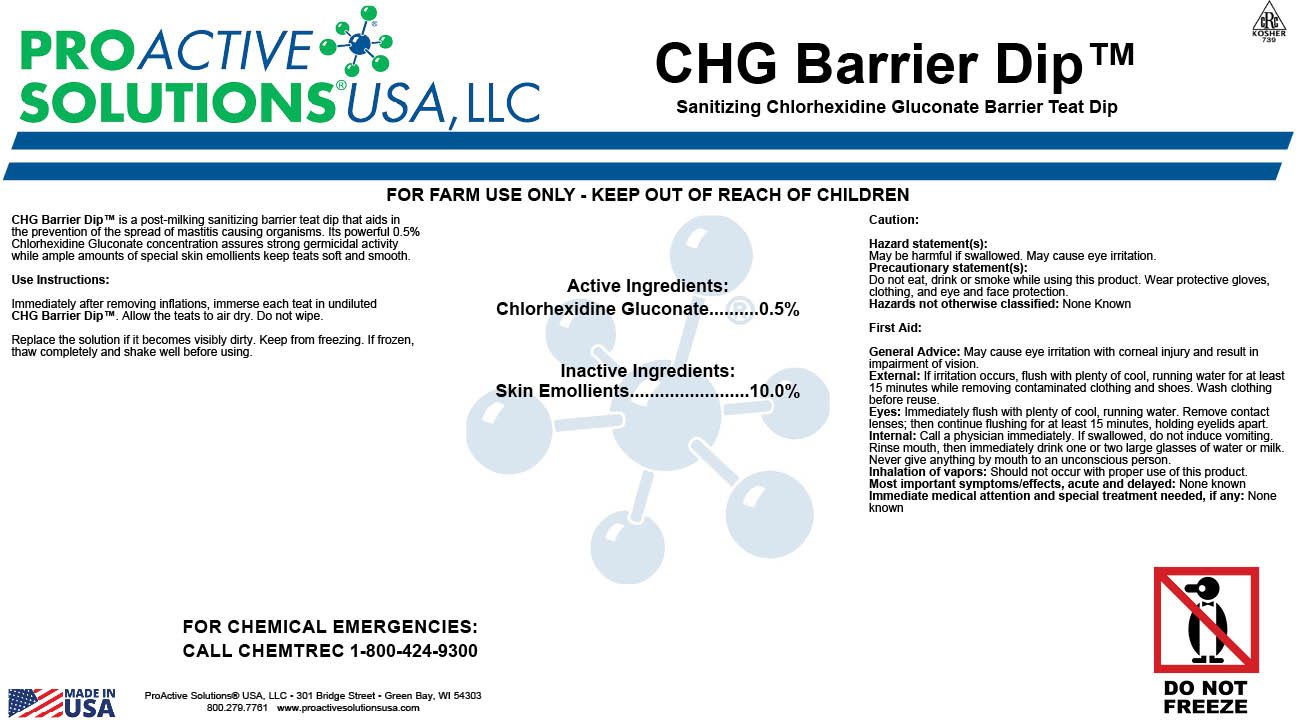 DRUG LABEL: CHG BARRIER DIP
NDC: 63927-4109 | Form: LIQUID
Manufacturer: ProActive Solutions USA, LLC
Category: animal | Type: OTC ANIMAL DRUG LABEL
Date: 20231219

ACTIVE INGREDIENTS: CHLORHEXIDINE GLUCONATE 0.5 kg/100 kg

CHG BARRIER DIP

CHG Barrier Dip™ is a post-milking sanitizing barrier teat dip that aids in
the prevention of the spread of mastitis causing organisms. Its powerful 0.5%
Chlorhexidine Gluconate concentration assures strong germicidal activity while ample
amounts of special skin emollients keep teats soft and smooth.

Use Instructions:

Immediately after removing inflations, immerse each teat in undiluted
CHG Barrier Dip™. Allow the teats to air dry. Do not wipe.

Replace the solution if it becomes visibly dirty. Keep from freezing. If frozen, thaw
completely and shake well before using.

Caution:

Hazard statement(s):
May be harmful if swallowed. May cause eye irritation.
Precautionary statement(s):
Do not eat, drink or smoke while using this product. Wear protective gloves, clothing, and
eye and face protection.
Hazards not otherwise classified: None Known

First Aid:

General Advice: May cause eye irritation with corneal injury and result in impairment of
vision.
External: If irritation occurs, flush with plenty of cool, running water for at least 15 minutes
while removing contaminated clothing and shoes. Wash clothing before reuse.
Eyes: Immediately flush with plenty of cool, running water. Remove contact lenses; then
continue flushing for at least 15 minutes, holding eyelids apart.
Internal: Call a physician immediately. If swallowed, do not induce vomiting. Rinse mouth,
then immediately drink one or two large glasses of water or milk. Never give anything by
mouth to an unconscious person.
Inhalation of vapors: Should not occur with proper use of this product.
Most important symptoms/effects, acute and delayed: None known
Immediate medical attention and special treatment needed, if any: None known